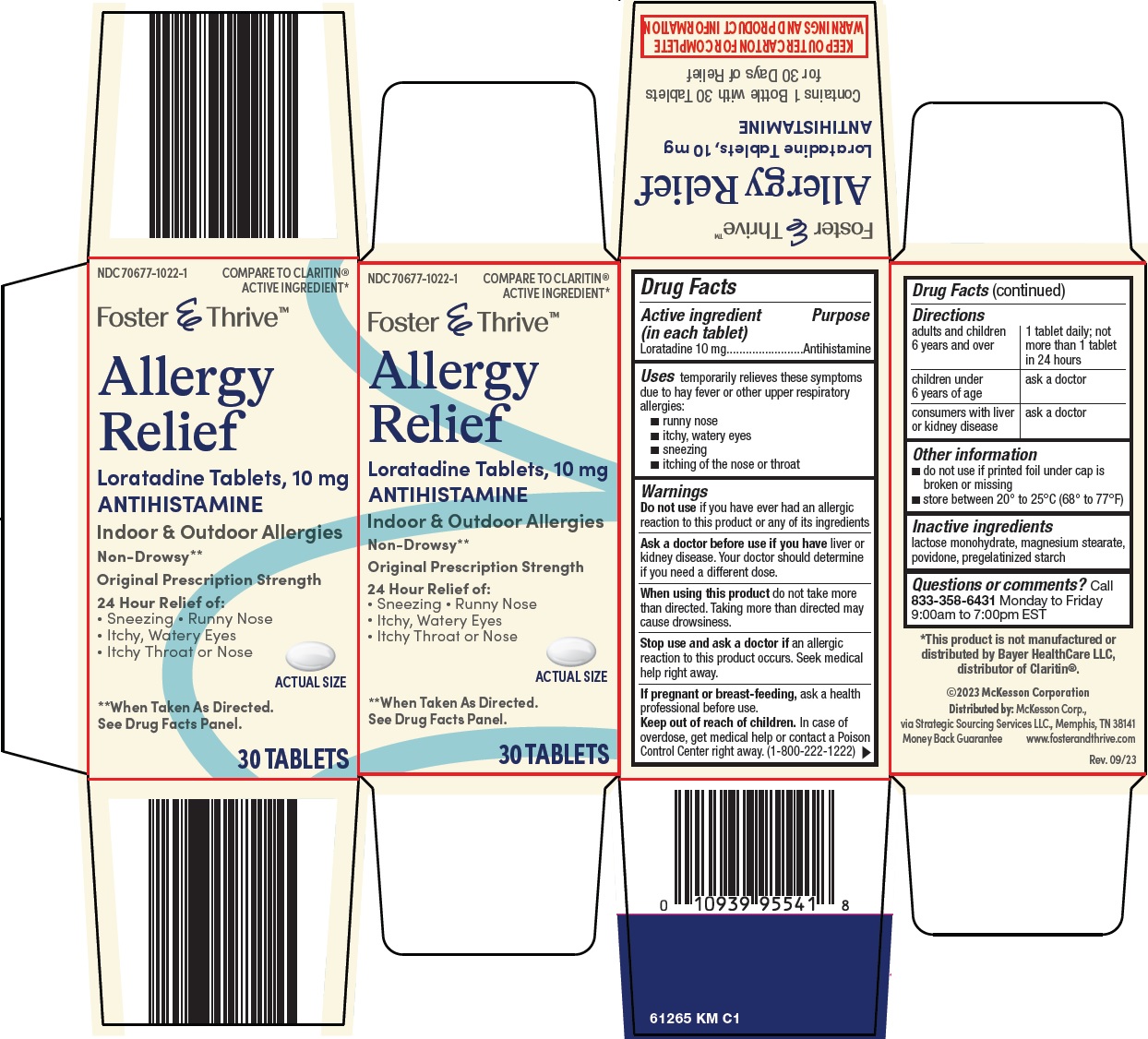 DRUG LABEL: foster and thrive allergy relief
NDC: 70677-1022 | Form: TABLET
Manufacturer: Strategic Sourcing Services LLC
Category: otc | Type: HUMAN OTC DRUG LABEL
Date: 20241211

ACTIVE INGREDIENTS: LORATADINE 10 mg/1 1
INACTIVE INGREDIENTS: LACTOSE MONOHYDRATE; MAGNESIUM STEARATE; POVIDONE, UNSPECIFIED

McKesson Allergy Relief Drug Facts

Active ingredient (in each tablet)

Loratadine 10 mg

Purpose

Antihistamine

Uses

temporarily relieves these symptoms due to hay fever or other upper respiratory allergies:

- runny nose
- itchy, watery eyes
- sneezing
- itching of the nose or throat

Warnings

Do not use

if you have ever had an allergic reaction to this product or any of its ingredients

Ask a doctor before use if you have

liver or kidney disease. Your doctor should determine if you need a different dose.

When using this product

do not take more than directed. Taking more than directed may cause drowsiness.

Stop use and ask a doctor if

an allergic reaction to this product occurs. Seek medical help right away.

If pregnant or breast-feeding,

ask a health professional before use.

Keep out of reach of children.

In case of overdose, get medical help or contact a Poison Control Center right away. (1-800-222-1222)

Directions

adults and children 6 years and over | 1 tablet daily; not more than 1 tablet in 24 hours
children under 6 years of age | ask a doctor
consumers with liver or kidney disease | ask a doctor

Other information

- do not use if printed foil under cap is broken or missing
- store between 20° to 25°C (68° to 77°F)

Inactive ingredients

lactose monohydrate, magnesium stearate, povidone, pregelatinized starch

Questions or comments?

Call 833-358-6431 Monday to Friday 9:00am to 7:00pm EST

Principal Display Panel

COMPARE TO CLARITIN® ACTIVE INGREDIENT

Foster & Thrive™

Allergy Relief

Loratadine Tablets, 10 mg

ANTIHISTAMINE

Indoor & Outdoor Allergies

Non-Drowsy**

Original Prescription Strength

24 Hour Relief of:

• Sneezing

• Runny Nose

• Itchy, Watery Eyes

• Itchy Throat or Nose

ACTUAL SIZE

**When Taken As Directed.

See Drug Facts Panel.

30 TABLETS